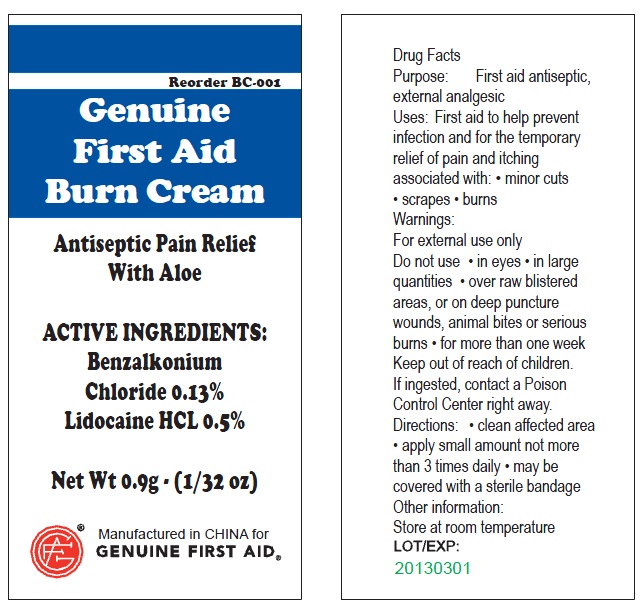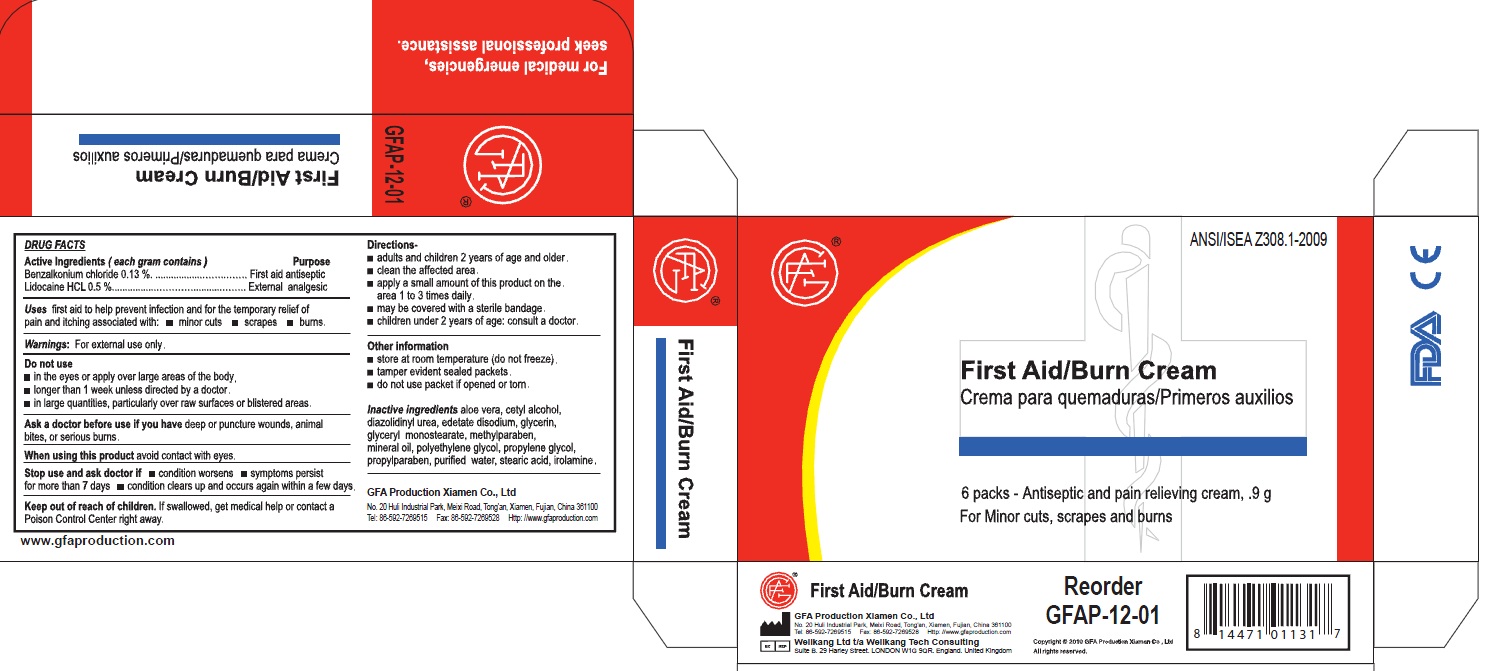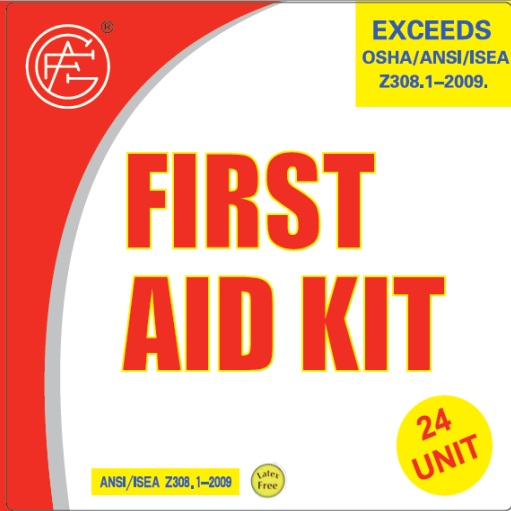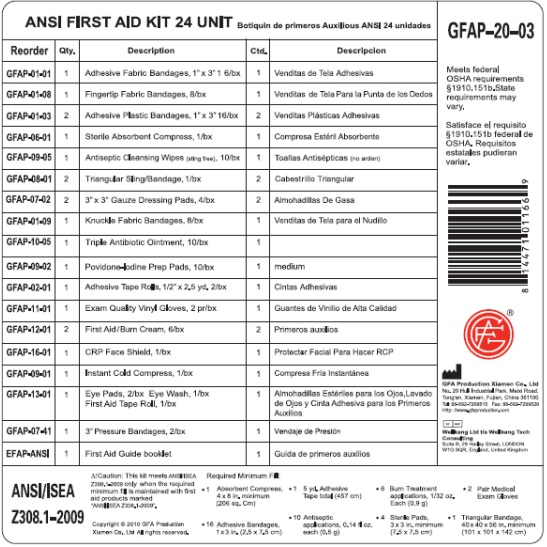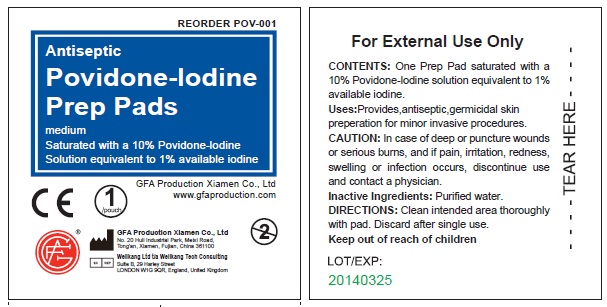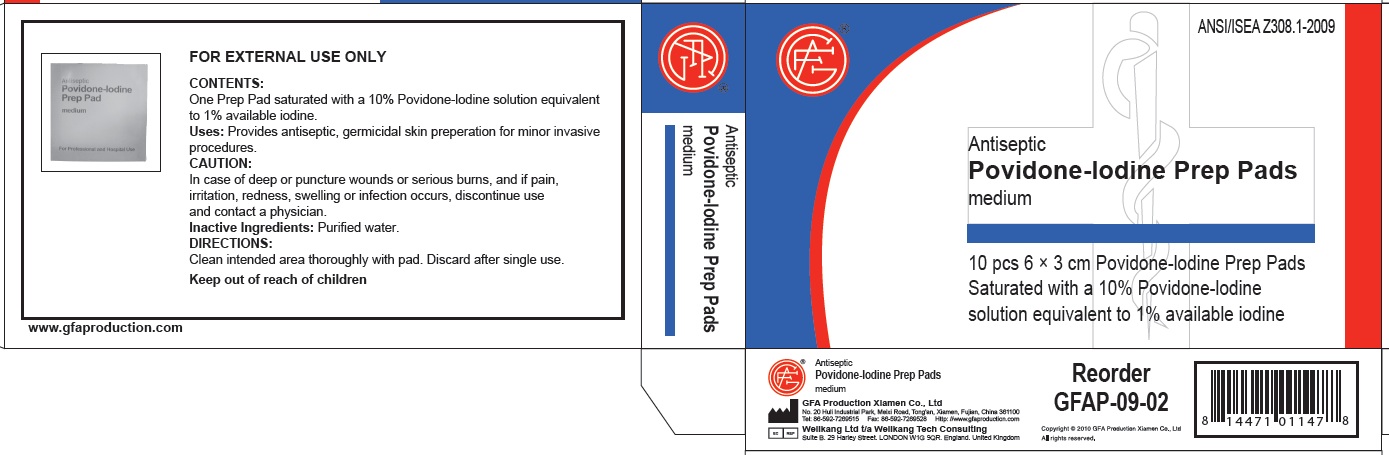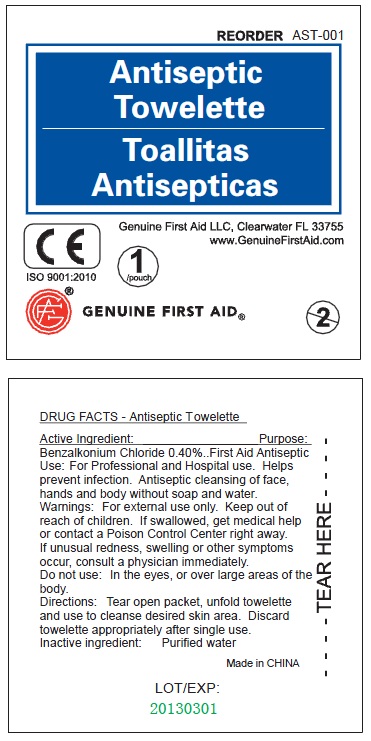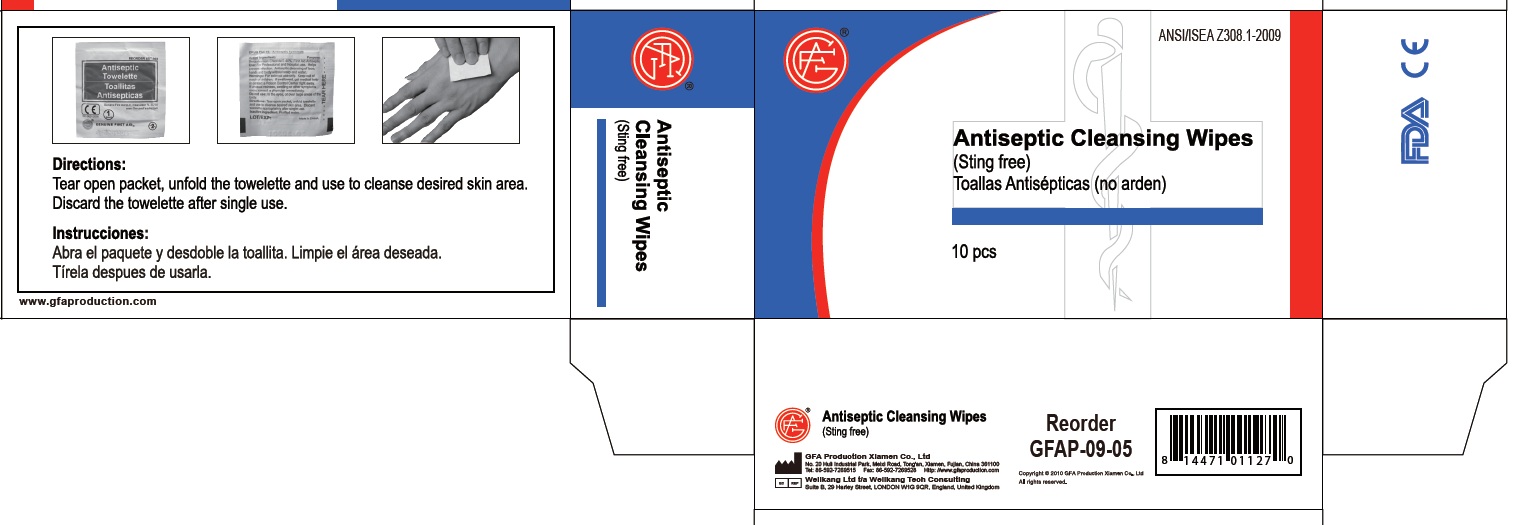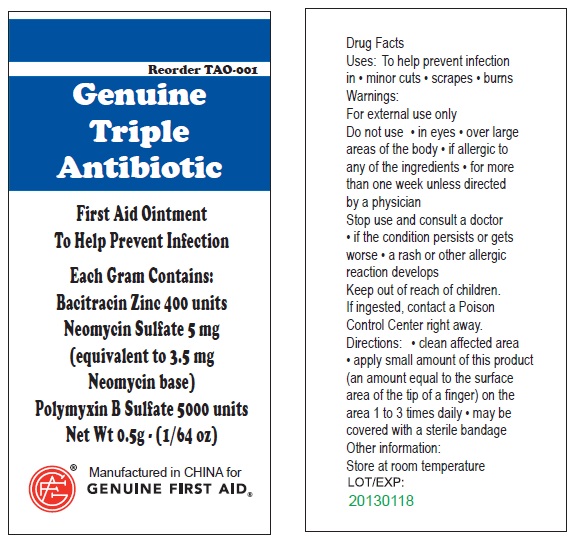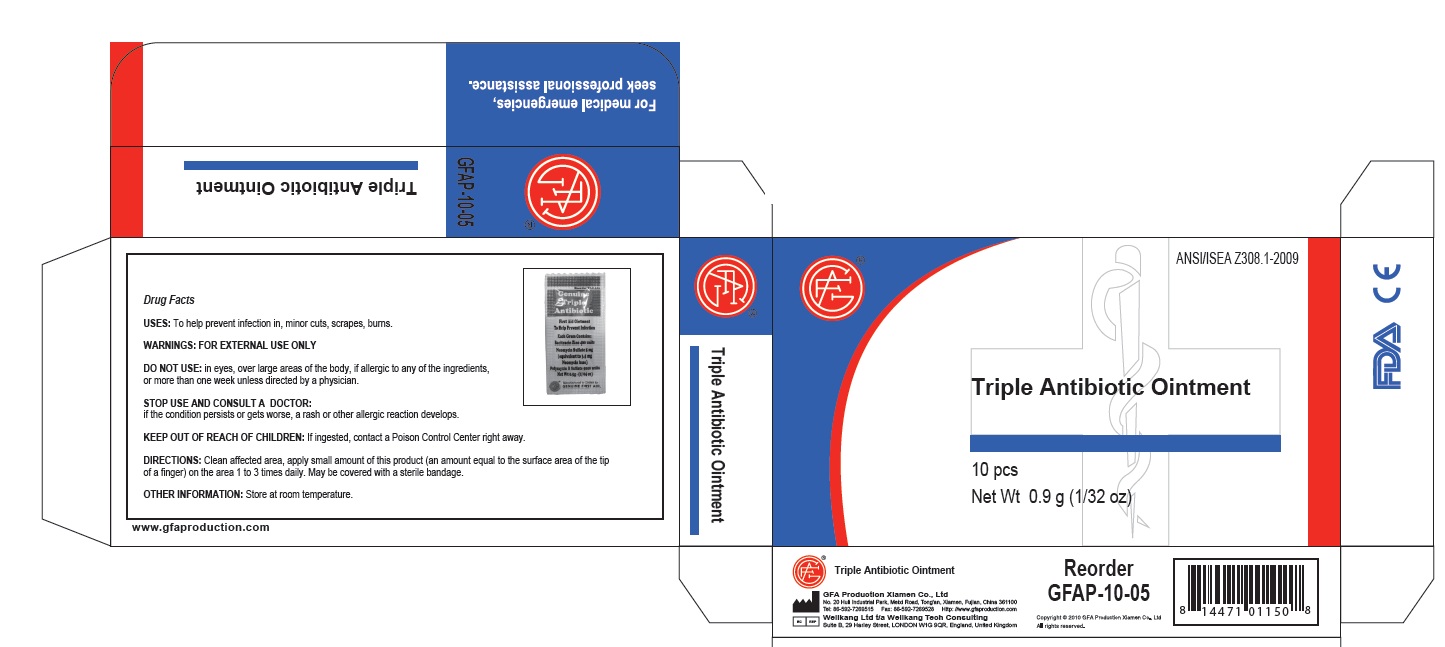 DRUG LABEL: GFA First Aid
NDC: 52124-1166 | Form: KIT | Route: TOPICAL
Manufacturer: Genuine First Aid, LLC
Category: otc | Type: HUMAN OTC DRUG LABEL
Date: 20110504

ACTIVE INGREDIENTS: BENZALKONIUM CHLORIDE 0.4 mL/100 mL; BENZALKONIUM CHLORIDE 0.13 g/100 g; LIDOCAINE 0.5 g/100 g; BACITRACIN ZINC 400 [iU]/1 g; NEOMYCIN SULFATE 5 mg/1 g; POLYMYXIN B SULFATE 5000 [iU]/1 g; POVIDONE-IODINE 1 mL/100 mL
INACTIVE INGREDIENTS: WATER; ALOE VERA LEAF; CETYL ALCOHOL; DIAZOLIDINYL UREA; EDETATE DISODIUM; GLYCERIN; GLYCERYL MONOSTEARATE; METHYLPARABEN; MINERAL OIL; POLYETHYLENE GLYCOL; PROPYLENE GLYCOL; PROPYLPARABEN; WATER; STEARIC ACID; WATER; WATER

GFA First Aid Kit

Active Ingredient

Benzalkonium Chloride 0.40%

Purpose

Antiseptic

Use

For Professional and Hospital use. Helps prevent infection. Antiseptic cleansing of face, hands and body without soap and water.

Warnings

Warning: For external use only.

Keep out of reach of children: If swallowed, get medical help or contact a Poison Control Center right away.

Stop use if unusual redness, swelling or other symptoms occur. Consult a physician immediately.

Do not use in the eyes or over large areas of the body.

Directions

Tear open packet, unfold towelette and use to cleanse desired skin area. Discard towelette appropriately after single use.

Inactive Ingredients

Inactive Ingredient: Purified water

LOT/EXP: Made in CHINA

20130301

PACKAGE LABEL

Antiseptic Towelette

Genuine First Aid LLC, Clearwater FL 33755

www.GenuineFirstAid.com

1/pouch

GENUINE FIRST AID

Active Ingredients

Benzalkonium Chloride 0.13%
Lidocaine HCL 0.5%

Purpose

Purpose: First aid antiseptic, external analgesic

Uses

First aid to help prevent infection and for the temporary relief of pain and itching associated with:

Minor Cuts

Scrapes

Burns

Warnings

For external use only

Do not use: In eyes, in large quantities, over raw blistered areas, or on deep puncture wounds, animal bites or serious burns, for more than one week
Do not use:
in the eyes or apply over large areas of the body.
longer than 1 week unless directed by a doctor.
in large quantities, particularly over raw surfaces or blistered areas.
Ask a doctor before use if you have deep puncture wounds, animal bites or serious burns.
When using this product, avoid contact with the eyes.

Stop use and ask a doctor if
condition worsens
symptoms persist for more than 7 days
condition clears up and occurs again within a few days

Keep out of reach of Children.
If ingested, contact a Poison Control Center right away.

Directions

Adults and children 2 years of age and older

clean affected area.

apply a small amount of this product on the area 1 to 3 times daily.

may be covered with a sterile bandage

children under 2 years of age: consult a doctor

Other Information:
Store at room temperature (do not freeze).

Taper evident sealed packets.

Do not use packet if opened or torn.

Inactive Ingredients

Aloe vera, cetyl alcohol, diazolidinyl urea, edetate disodium, glycerin, glyceryl monostearate, methylparaben, mineral oil, polyethylene glycol, propylene glycol, propylparaben, purified water, stearic acid, irolamine

DESCRIPTION

LOT/EXP: Made in CHINA
20130301

GFA Production Xiamen Co., Ltd
No. 20 Huli Industrial Park, Meixi Road, Tong'an, Xiamen, Fujian, China 361100
Tel: 86-592-7269515 Fax: 86-592-7269528 Http: //www.gfaproduction.com

PACKAGE LABEL

Genuine First Aid Burn Cream
Antiseptic Pain Relief With Aloe
Net Wt 0.9g (1/32 oz)
Manufactured in CHINA for
Genuine First Aid.

Active Ingredients

Active Ingredient: .........Bacitracin Zinc 400 units

Neomycin Sulfate 5mg (equivalent to 3.5 mg Neomycin base)

Polymyxin B Sulfate 5000 units

Purpose

Triple Antibiotic

INDICATIONS AND USAGE

Uses: To help prevent infection in:
minor cuts; scrapes; burns

Warnings

For external use only.

Do not use: in eyes; over large areas of the body;

If allergic to any of the ingredients; for more than one week unless directed by a physician.

Stop use and consult a doctor:

if the condition persists or gets worse; a rash or other allergic reaction develops

Keep out of reach of children.

If ingested, contact a Poison

Control Center right away.

Directions

Directions: clean affected area; apply small amount of this product (an amount equal to the surface area of the tip of a finger) on the area 1 to 3 times daily; may be covered with a sterile bandage

Other information:

Store at room temperature.

Inactive Ingredient

water

PACKAGE LABEL

Genuine Triple Antibiotic

First Aid Ointment

To Help Prevent Infection

Each Gram Contains:

Bacitracin Zinc 400 units

Neomycin Sulfate 5 mg

(equivalent to 3.5 mg

Neomycin base)

Polymyxin B Sulfate 5000 units

Net Wt. 0.5g ; (1/64 oz)

Manufactured in CHINA for

GENUINE FIRST AID.

Triple Antibiotic Ointment 10pcs

Net wt. 0.9g (1/32oz)

100
Triple Antibiotic

Active Ingredient

One Prep pad saturated with a 10% Povidone-Iodine solution equivalent to 1% available iodine

Purpose

antiseptic, germicidal

Uses

Provides, antiseptic germicidal skin preperation for minor invasive procedures

Keep out of reach of children

For external use only.

Caution

In case of deep or puncture wounds or serious burns, and if pain, irritation, redness, swelling or infection occurs, discontinue use and contact a physician.

Inactive Ingredients

Purified water.

Directions

Clean intended area thoroughly with pad. Discard after single use.

PACKAGE LABEL

Antiseptic
Povidone-Iodine
Prep Pads
medium
Saturated with a 10% Povidone-Iodine
Solution equavalent to 1% available iodine
GFA Production Xiamen Co., Ltd.
www.gfaproduction.com
GFA Production Xiamen Co., Ltd.
No. 20 Huli Industrial Park, Meixi Road,
Tong'an, Xiamen, Fujian, China 361100
Wellkang Ltd t/a Wellkang Tech Consulting
Suite B, 29 Harley Street
LONDON W1G 9QR, England, United Kingdom